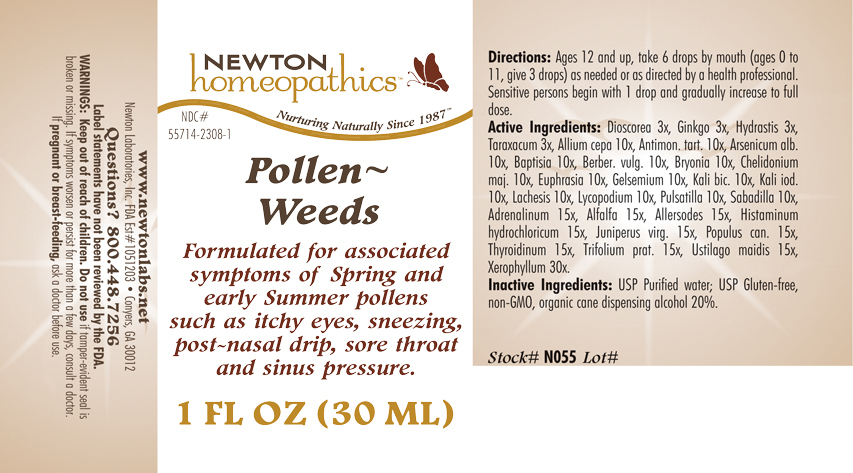 DRUG LABEL: Pollen Weeds 
NDC: 55714-2308 | Form: LIQUID
Manufacturer: Newton Laboratories, Inc.
Category: homeopathic | Type: HUMAN OTC DRUG LABEL
Date: 20110301

ACTIVE INGREDIENTS: Xerophyllum Asphodeloides 30 [hp_X]/1 mL; Epinephrine 15 [hp_X]/1 mL; Alfalfa 15 [hp_X]/1 mL; Aletris Farinosa Root 15 [hp_X]/1 mL; Artemisia Vulgaris Root 15 [hp_X]/1 mL; Bellis Perennis 15 [hp_X]/1 mL; Dysphania Ambrosioides 15 [hp_X]/1 mL; Lycopus Virginicus 15 [hp_X]/1 mL; Phytolacca Americana Root 15 [hp_X]/1 mL; Populus Tremuloides Leaf 15 [hp_X]/1 mL; Populus Tremuloides Bark 15 [hp_X]/1 mL; Ptelea Trifoliata Bark 15 [hp_X]/1 mL; Sambucus Nigra Flowering Top 15 [hp_X]/1 mL; Trillium Erectum Root 15 [hp_X]/1 mL; Elymus Repens Root 15 [hp_X]/1 mL; Urtica Urens 15 [hp_X]/1 mL; Wyethia Helenioides Root 15 [hp_X]/1 mL; Yucca Filamentosa 15 [hp_X]/1 mL; Avena Sativa Pollen 15 [hp_X]/1 mL; Cynosurus Cristatus Pollen 15 [hp_X]/1 mL; Echinochloa Crus-galli Pollen 15 [hp_X]/1 mL; Poa Pratensis Pollen 15 [hp_X]/1 mL; Agrostis Gigantea Pollen 15 [hp_X]/1 mL; Bromus Secalinus Pollen 15 [hp_X]/1 mL; Alopecurus Pratensis Pollen 15 [hp_X]/1 mL; Phleum Pratense Pollen 15 [hp_X]/1 mL; Festuca Pratensis Pollen 15 [hp_X]/1 mL; Holcus Lanatus Pollen 15 [hp_X]/1 mL; Lolium Perenne Pollen 15 [hp_X]/1 mL; Fagus Sylvatica Pollen 15 [hp_X]/1 mL; Betula Pendula Pollen 15 [hp_X]/1 mL; Quercus Alba Pollen 15 [hp_X]/1 mL; Fraxinus Excelsior Pollen 15 [hp_X]/1 mL; Corylus Americana Pollen 15 [hp_X]/1 mL; Populus Nigra Pollen 15 [hp_X]/1 mL; Platanus Orientalis Pollen 15 [hp_X]/1 mL; Ulmus Glabra Pollen 15 [hp_X]/1 mL; Salix Alba Pollen 15 [hp_X]/1 mL; Narcissus Pseudonarcissus 15 [hp_X]/1 mL; Rosa Canina Flower 15 [hp_X]/1 mL; Lilium Candidum Flower 15 [hp_X]/1 mL; Primula Vulgaris 15 [hp_X]/1 mL; Dianthus Caryophyllus Flower 15 [hp_X]/1 mL; Ulex Europaeus Flower 15 [hp_X]/1 mL; Cytisus Scoparius Pollen 15 [hp_X]/1 mL; Calluna Vulgaris Pollen 15 [hp_X]/1 mL; Crataegus Monogyna Pollen 15 [hp_X]/1 mL; Histamine Dihydrochloride 15 [hp_X]/1 mL; Juniperus Virginiana Twig 15 [hp_X]/1 mL; Populus Balsamifera Leaf Bud 15 [hp_X]/1 mL; Thyroid, Unspecified 15 [hp_X]/1 mL; Trifolium Pratense Flower 15 [hp_X]/1 mL; Ustilago Maydis 15 [hp_X]/1 mL; Onion 10 [hp_X]/1 mL; Antimony Potassium Tartrate 10 [hp_X]/1 mL; Arsenic Trioxide 10 [hp_X]/1 mL; Baptisia Tinctoria Root 10 [hp_X]/1 mL; Berberis Vulgaris Root Bark 10 [hp_X]/1 mL; Bryonia Alba Root 10 [hp_X]/1 mL; Chelidonium Majus 10 [hp_X]/1 mL; Euphrasia Stricta 10 [hp_X]/1 mL; Gelsemium Sempervirens Root 10 [hp_X]/1 mL; Potassium Dichromate 10 [hp_X]/1 mL; Potassium Iodide 10 [hp_X]/1 mL; Lachesis Muta Venom 10 [hp_X]/1 mL; Lycopodium Clavatum Spore 10 [hp_X]/1 mL; Pulsatilla Vulgaris 10 [hp_X]/1 mL; Schoenocaulon Officinale Seed 10 [hp_X]/1 mL; Dioscorea Villosa Tuber 3 [hp_X]/1 mL; Ginkgo 3 [hp_X]/1 mL; Goldenseal 3 [hp_X]/1 mL; Taraxacum Officinale 3 [hp_X]/1 mL; Anthoxanthum Odoratum Pollen 15 [hp_X]/1 mL
INACTIVE INGREDIENTS: Water; Alcohol

Pollen - Weeds

INDICATIONS & USAGE SECTION

Pollen Weeds Formulated for associated symptoms of Spring and early Summer pollens such as itchy eyes, sneezing, post-nasal drip, sore throat and sinus pressure.

DOSAGE & ADMINISTRATION SECTION

Directions: Ages 12 and up, take 6 drops by mouth (ages 0 to 11, give 3 drops) as needed or as directed by a health professional. Sensitive persons begin with 1 drop and gradually increase to full dose.

OTC - ACTIVE INGREDIENT SECTION

Xerophyllum asphodeloides 30, Adrenalinum 15x, Alfalfa 15x, Allersodes 15x, Histaminum hydrochloricum 15x, Juniperus virg. 15x, Populus can. 15x, Thyroidinum 15x, Trifolium prat. 15x, Ustilago maidis 15x, Allium cepa 10x, Antimon. tart. 10x, Arsenicum alb. 10x, Baptisia 10x, Berber. vulg. 10x, Bryonia 10x, Chelidonium majus 10x, Euphrasia 10x, Gelsemium 10x, Kali bic. 10x, Kali iod. 10x, Lachesis 10x, Lycopodium 10x, Pulsatilla 10x, Sabadilla 10x, Dioscorea 3x, Ginkgo 3x, Hydrastis 3x, Taraxacum 3x.

OTC - PURPOSE SECTION

Formulated for associated symptoms of Spring and early Summer pollens such as itchy eyes, sneezing, post-nasal drip, sore throat and sinus pressure

INACTIVE INGREDIENT SECTION

Inactive Ingredients: USP Purified Water; USP Gluten-free, non-GMO, organic cane dispensing alcohol 20%.

QUESTIONS SECTION

www.newtonlabs.net Newton Laboratories, Inc. FDA Est # 1051203 - Conyers, GA 30012
Questions? 1.800.448.7256

WARNINGS SECTION

Warnings: Keep out of reach of children. Do no use if tamper-evident seal is broken or missing. If symptoms worsen or persist for more than a few days, consult a doctor. If pregnant or breast-feeding, ask a doctor before use.

OTC - PREGNANCY OR BREAST FEEDING SECTION

If pregnant or breast-feeding, ask a doctor before use.

OTC - KEEP OUT OF REACH OF CHILDREN SECTION

Keep out of reach of children.